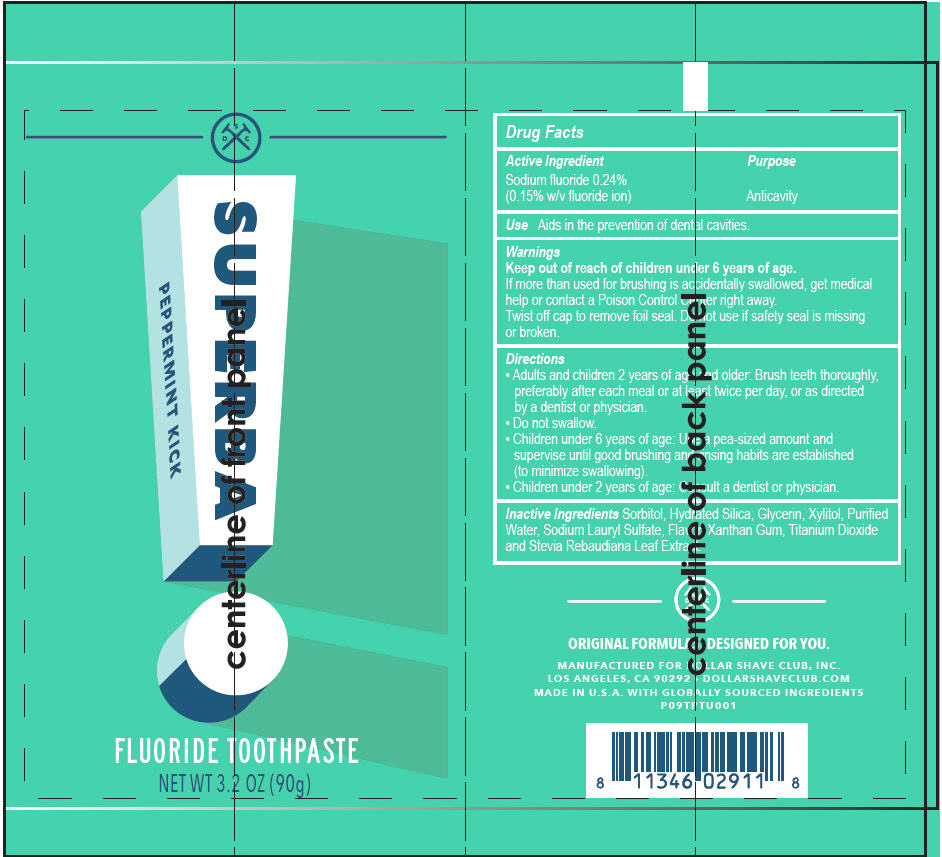 DRUG LABEL: Dollar Shave Club
NDC: 69522-1111 | Form: PASTE, DENTIFRICE
Manufacturer: Dollar Shave Club
Category: otc | Type: HUMAN OTC DRUG LABEL
Date: 20180108

ACTIVE INGREDIENTS: Sodium fluoride 1.5 mg/1 g
INACTIVE INGREDIENTS: Sorbitol; Hydrated silica; water; Xylitol; Glycerin; Xanthan Gum; Titanium Dioxide; Sodium lauryl sulfate; Stevia Rebaudiuna Leaf

Dollar Shave Club

Drug Facts

Active Ingredient

Sodium fluoride 0.24%
(0.15% w/v fluoride ion)

Purpose

Anticavity

Use

Aids in the prevention of dental cavities.

Warnings

Keep out of reach of children under 6 years of age.

If more than used for brushing is accidentally swallowed, get medical help or contact a Poison Control Center right away.

DO NOT USE

Twist off cap to remove foil seal. Do not use if safety seal is missing or broken.

Directions

- Adults and children 2 years of age and older: Brush teeth thoroughly, preferably after each meal or at least twice per day, or as directed by a dentist or physician.
- Do not swallow.
- Children under 6 years of age: Use a pea-sized amount and supervise until good brushing and rinsing habits are established (to minimize swallowing).
- Children under 2 years of age: Consult a dentist or physician.

Inactive Ingredients

Sorbitol, Hydrated Silica, Glycerin, Xylitol, Purified Water, Sodium Lauryl Sulfate, Flavor, Xanthan Gum, Titanium Dioxide and Stevia Rebaudiana Leaf Extract.

PRINCIPAL DISPLAY PANEL - 90 g Tube Label

SUPERBA

PEPPERMINT KICK

FLUORIDE TOOTHPASTE

NET WT 3.2 OZ (90g)